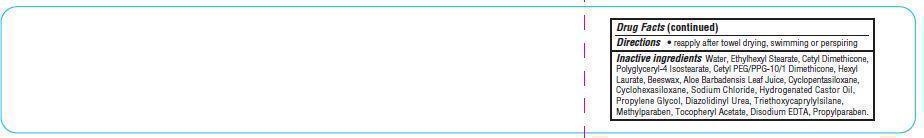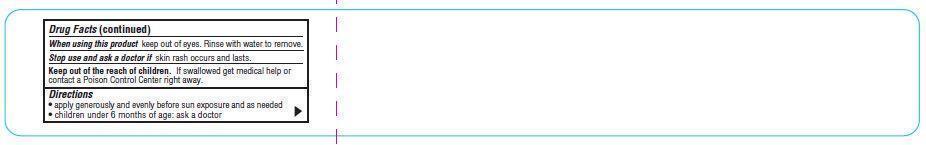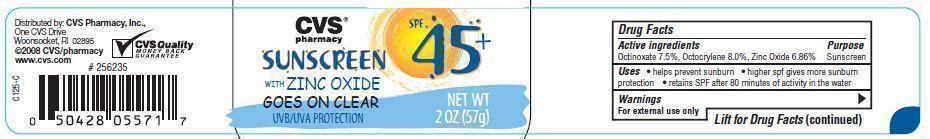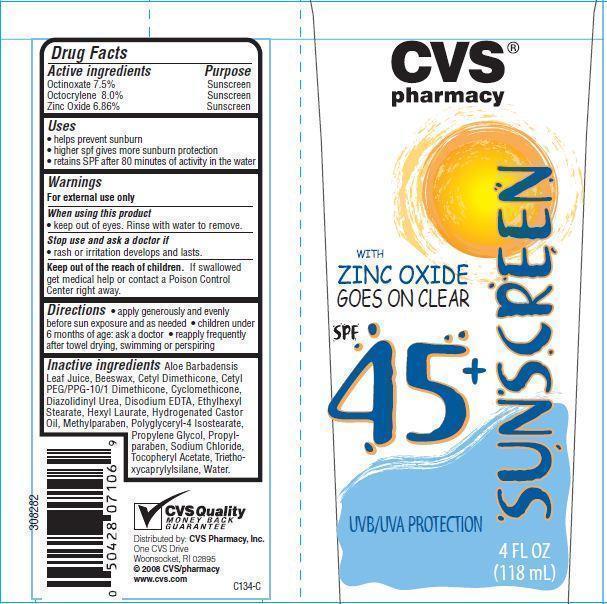 DRUG LABEL: CVS Pharmacy Sunscreen SPF 45
                
NDC: 59779-020 | Form: LOTION
Manufacturer: CVS Pharmacy
Category: otc | Type: HUMAN OTC DRUG LABEL
Date: 20121217

ACTIVE INGREDIENTS: OCTINOXATE 7.5 g/100 g; OCTOCRYLENE 8 g/100 g; ZINC OXIDE 6.8 g/100 g
INACTIVE INGREDIENTS: ALOE VERA LEAF; YELLOW WAX; CYCLOMETHICONE; DIAZOLIDINYL UREA; EDETATE DISODIUM; ETHYLHEXYL STEARATE; HEXYL LAURATE; HYDROGENATED CASTOR OIL; METHYLPARABEN; POLYGLYCERYL-4 ISOSTEARATE; PROPYLENE GLYCOL; PROPYLPARABEN; SODIUM CHLORIDE; .ALPHA.-TOCOPHEROL ACETATE; TRIETHOXYCAPRYLYLSILANE; WATER

Drug Facts

Active ingredients

Octinoxate 7.5%
Octocrylene 8.0%
Zinc Oxide 6.86%

Purpose

Sunscreen

Uses

- helps prevent sunburn
- higher SPF gives more sunburn protection
- retains SPF after 80 minutes of activity in water

Warnings

For external use only

When using this product

- keep out of eyes. Rinse with water to remove.

Stop use and ask a doctor if

- rash or irritation develops and lasts.

Keep out of the reach of children.
If swallowed get medical help or contact a Poison Control Center right away.

Directions

- apply generously and evenly before sun exposure and as needed
- children under 6 months of age: ask a doctor
- reapply frequently and after towel drying, swimming or perspiring

Other information

- may stain some materials

Inactive ingredients

Water, Ethylhexyl Stearate, Cetyl Dimethicone, Polyglyceryl-4 Isostearate, Cetyl PEG/PPG-10/1 Dimethicone, Hexyl Laurate, Beeswax, Hydrogenated Castor Oil, Sodium Chloride, Cyclopentasiloxane, Propylene Glycol, Cyclohexasiloxane, Triethoxycaprylylsilane, Tocopheryl Acetate, Aloe Barbadensis Leaf Juice, Diazolidinyl Urea, Methylparaben, Disodium EDTA, Propylparaben

Principal Display Panel

CVS
pharmacy
SUNSCREEN
WITH
ZINC OXIDE
GOES ON CLEAR
SPF 45+
UVA/UVB PROTECTION
4 FL OZ(118 mL)
CVS
pharmacy
SUNSCREEN
WITH
ZINC OXIDE
GOES ON CLEAR
SPF 45+
UVA/UVB PROTECTION
NET WT 2 FL OZ(59 mL)